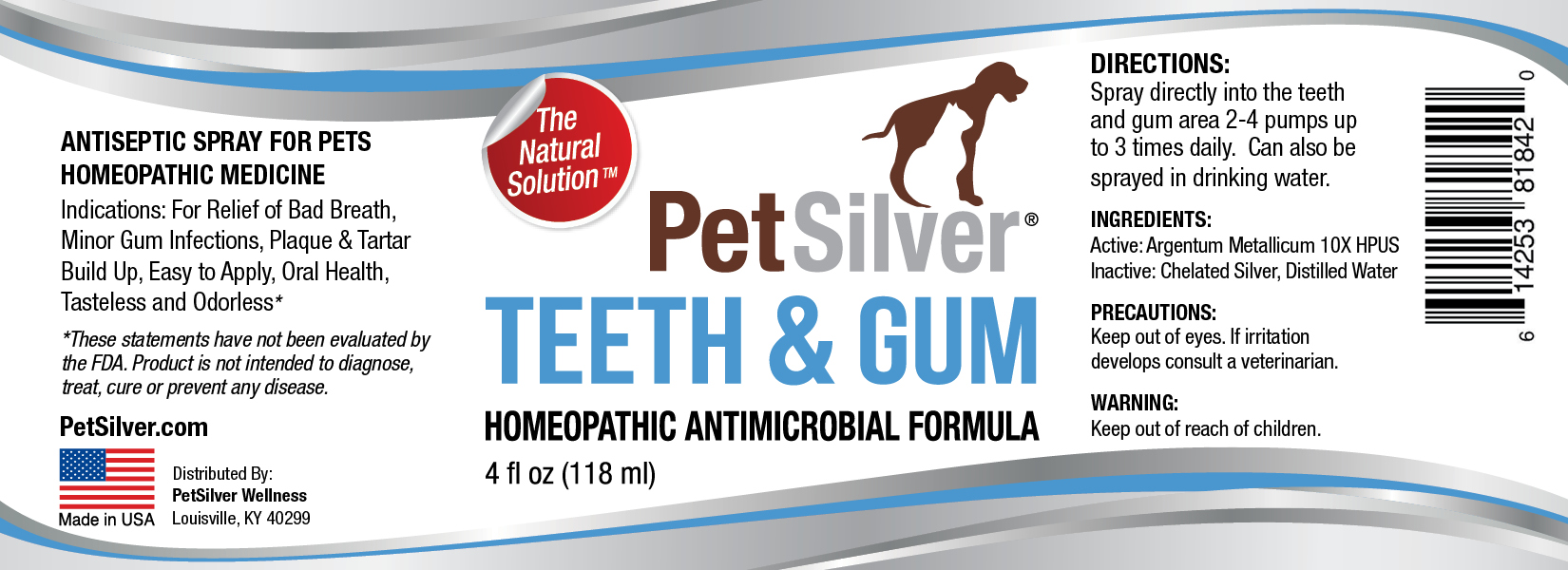 DRUG LABEL: PetSilver Teeth and Gum
NDC: 72363-021 | Form: SPRAY
Manufacturer: AG Essence
Category: homeopathic | Type: HUMAN OTC DRUG LABEL
Date: 20251214

ACTIVE INGREDIENTS: SILVER 0.0035 g/118 g
INACTIVE INGREDIENTS: ANHYDROUS CITRIC ACID 0.018 g/118 g; WATER 117.9785 g/118 g

PetSilver Teeth & Gum 4 ounces

DIRECTIONS:

Clean area of dirt and debris. Apply 3-4 sprays to affected area up to 3 times daily. Dress area if needed. Consult your veterinarian if problem persists.

PRECAUTIONS:

Keep out of eyes. If irritation develops consult a veterinarian.

INGREDIENT:

Active: Argentum Metallicum10X HPUS

INGREDIENTS:

Inactive: Chelated Silver, Distilled Water

Indications:

For relief of skin irritations, minor wounds, burns, minor infections, hot spots, scrapes and insect bites.

WARNING:

Keep out of reach of children.

WARNING:

Keep out of reach of children